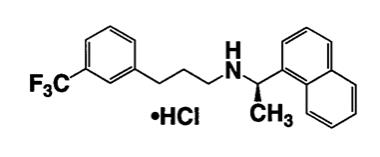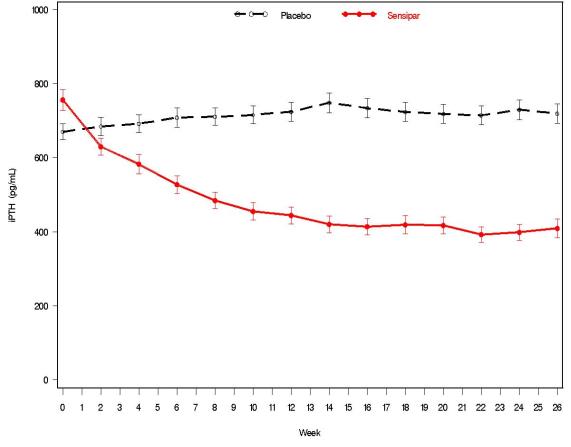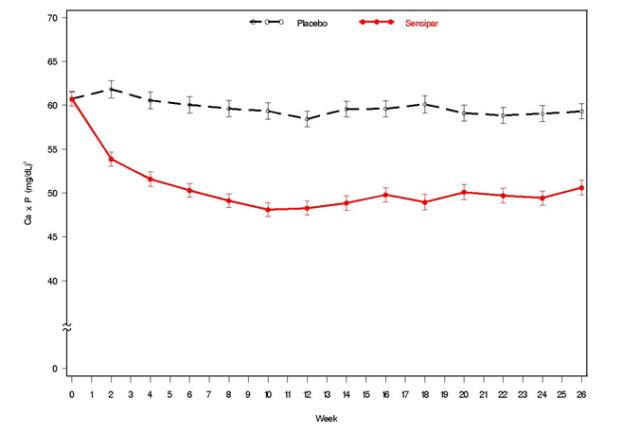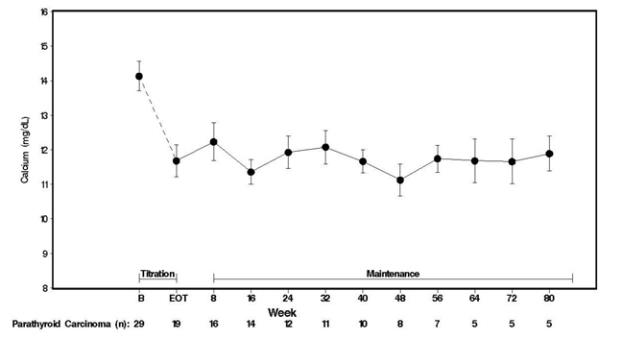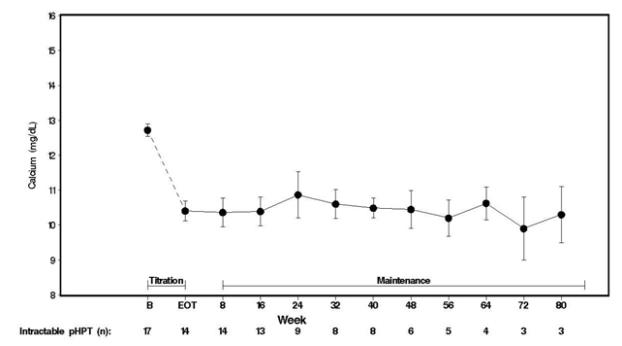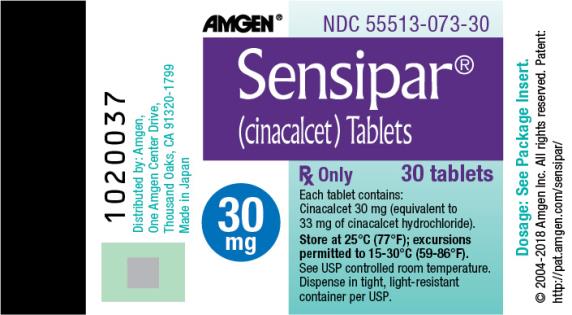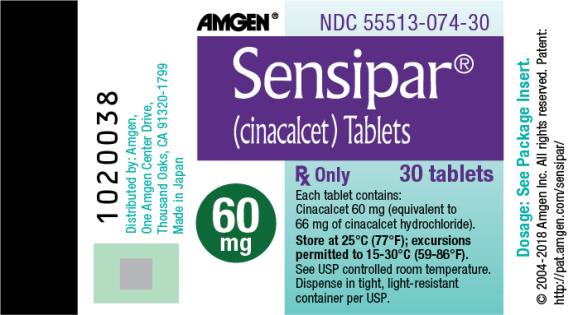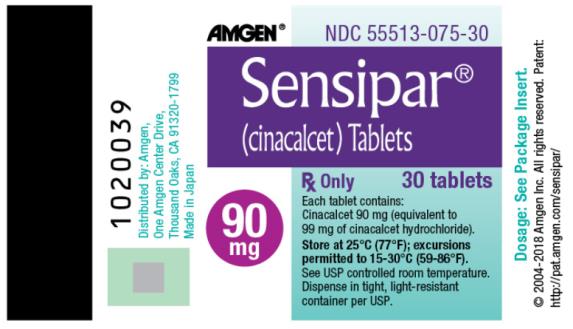 DRUG LABEL: Sensipar
NDC: 55513-073 | Form: TABLET, COATED
Manufacturer: Amgen Inc
Category: prescription | Type: HUMAN PRESCRIPTION DRUG LABEL
Date: 20251207

ACTIVE INGREDIENTS: CINACALCET HYDROCHLORIDE 30 mg/1 1
INACTIVE INGREDIENTS: CARNAUBA WAX; MICROCRYSTALLINE CELLULOSE; CROSPOVIDONE, UNSPECIFIED; MAGNESIUM STEARATE; POVIDONE, UNSPECIFIED; STARCH, CORN; SILICON DIOXIDE

HIGHLIGHTS OF PRESCRIBING INFORMATION

These highlights do not include all the information needed to use SENSIPAR safely and effectively. See full prescribing information for SENSIPAR.
SENSIPAR® (cinacalcet) tablets, for oral use
Initial U.S. Approval: 2004

1 INDICATIONS AND USAGE

Sensipar is a positive modulator of the calcium sensing receptor indicated for:

- Secondary Hyperparathyroidism (HPT) in adult patients with chronic kidney disease (CKD) on dialysis. (1.1)
  Limitations of Use: Sensipar is not indicated for use in patients with CKD who are not on dialysis

- Hypercalcemia in adult patients with Parathyroid Carcinoma (PC). (1.2)
- Hypercalcemia in adult patients with primary HPT for whom parathyroidectomy would be indicated on the basis of serum calcium levels, but who are unable to undergo parathyroidectomy. (1.3)

2 DOSAGE AND ADMINISTRATION

- Sensipar tablets should be taken with food or shortly after a meal (2.1)
- Tablets should always be taken whole and not divided (2.1)
- Secondary HPT in patients with CKD on dialysis (2.2):
  ○ Starting dose is 30 mg once daily.
  ○ Titrate dose no more frequently than every 2 to 4 weeks through sequential doses of 30, 60, 90, 120, and 180 mg once daily as necessary to achieve targeted intact parathyroid hormone (iPTH) levels.
  ○ iPTH levels should be measured no earlier than 12 hours after most recent dose.
- Hypercalcemia in patients with PC or hypercalcemia in patients with primary HPT (2.3):
  ○ Starting dose is 30 mg twice daily.
  ○ Titrate dose every 2 to 4 weeks through sequential doses of 30 mg twice daily, 60 mg twice daily, 90 mg twice daily, and 90 mg three or four times daily as necessary to normalize serum calcium levels.
- Once the maintenance dose has been established, monitor serum calcium approximately monthly for patients with secondary HPT and every 2 months for patients with PC or primary HPT (2.4)

3 DOSAGE FORMS AND STRENGTHS

- Tablets: 30, 60, and 90 mg tablets (3)

4 CONTRAINDICATIONS

Sensipar treatment initiation is contraindicated if serum calcium is less than the lower limit of the normal range. (4, 5.1)

5 WARNINGS AND PRECAUTIONS

- Hypocalcemia: Life threatening events and fatal outcomes were reported. Hypocalcemia can prolong QT interval, lower the threshold for seizures, and cause hypotension, worsening heart failure, and/or arrhythmia. Monitor serum calcium carefully for the occurrence of hypocalcemia during treatment. (2.4, 5.1)
- Upper Gastrointestinal (GI) Bleeding: Patients with risk factors for upper GI bleeding may be at increased risk. Monitor patients and promptly evaluate and treat any suspected GI bleeding. (5.2)
- Hypotension, Worsening Heart Failure and/or Arrhythmias: In postmarketing safety surveillance, isolated, idiosyncratic cases of hypotension, worsening heart failure, and/or arrhythmia have been reported in patients with impaired cardiac function. (5.3)
- Adynamic Bone Disease: May develop if iPTH levels are suppressed below 100 pg/mL. (5.4)

6 ADVERSE REACTIONS

The most common adverse reactions (i.e., ≥ 25%) associated with Sensipar were nausea and vomiting. (6)

To report SUSPECTED ADVERSE REACTIONS, contact Amgen Medical Information at 1-800-77-AMGEN (1-800-772-6436) or FDA at 1-800-FDA-1088 or www.fda.gov/medwatch.

7 DRUG INTERACTIONS

- Co-administration with a strong CYP3A4 inhibitor may increase serum levels of cinacalcet. Dose adjustment and monitoring of iPTH serum phosphorus and serum calcium may be required. (7.1)
- Cinacalcet is a strong inhibitor of CYP2D6. Dose adjustments may be required for concomitant medications that are predominantly metabolized by CYP2D6. (7.2)

8 USE IN SPECIFIC POPULATIONS

- Pediatric Use: A fatal outcome was reported in a pediatric clinical trial patient with severe hypocalcemia. Sensipar is not indicated for use in pediatric patients. (8.4)

FULL PRESCRIBING INFORMATION

1 INDICATIONS AND USAGE

1.1 Secondary Hyperparathyroidism

Sensipar is indicated for the treatment of secondary hyperparathyroidism (HPT) in adult patients with chronic kidney disease (CKD) on dialysis [see Clinical Studies (14.1)].

Limitations of Use:

Sensipar is not indicated for use in patients with CKD who are not on dialysis because of an increased risk of hypocalcemia [see Warnings and Precautions (5.1)].

1.2 Parathyroid Carcinoma

Sensipar is indicated for the treatment of hypercalcemia in adult patients with Parathyroid Carcinoma [see Clinical Studies (14.2)].

1.3 Primary Hyperparathyroidism

Sensipar is indicated for the treatment of hypercalcemia in adult patients with primary HPT for whom parathyroidectomy would be indicated on the basis of serum calcium levels, but who are unable to undergo parathyroidectomy [see Clinical Studies (14.3)].

2 DOSAGE AND ADMINISTRATION

2.1 Administration

Sensipar should be taken with food or shortly after a meal.

Sensipar tablets are administered orally and should always be taken whole and not chewed, crushed, or divided.

2.2 Secondary Hyperparathyroidism in Patients with Chronic Kidney Disease on Dialysis

The recommended starting oral dose of Sensipar is 30 mg once daily. Serum calcium and serum phosphorus should be measured within 1 week and intact parathyroid hormone (iPTH) should be measured 1 to 4 weeks after initiation or dose adjustment of Sensipar [see Dosage and Administration (2.3)]. Sensipar should be titrated no more frequently than every 2 to 4 weeks through sequential doses of 30, 60, 90, 120, and 180 mg once daily to target iPTH levels of 150 to 300 pg/mL. Serum iPTH levels should be assessed no earlier than 12 hours after dosing with Sensipar.

Sensipar can be used alone or in combination with vitamin D sterols and/or phosphate binders.

During dose titration, serum calcium levels should be monitored frequently and if levels decrease below the normal range, appropriate steps should be taken to increase serum calcium levels, such as by providing supplemental calcium, initiating or increasing the dose of calcium-based phosphate binder, initiating or increasing the dose of vitamin D sterols, or temporarily withholding treatment with Sensipar [see Dosage and Administration (2.4) and Warnings and Precautions (5.1)].

2.3 Patients with Parathyroid Carcinoma and Primary Hyperparathyroidism

The recommended starting oral dose of Sensipar is 30 mg twice daily.

The dose of Sensipar should be titrated every 2 to 4 weeks through sequential doses of 30 mg twice daily, 60 mg twice daily, and 90 mg twice daily, and 90 mg 3 or 4 times daily as necessary to normalize serum calcium levels. Serum calcium should be measured within 1 week after initiation or dose adjustment of Sensipar [see Dosage and Administration (2.4) and Warnings and Precautions (5.1)].

2.4 Switching from Parsabiv (etelcalcetide) to Sensipar

Discontinue etelcalcetide for at least 4 weeks prior to starting Sensipar. Ensure corrected serum calcium is at or above the lower limit of normal prior to Sensipar initiation [see Warnings and Precautions (5.1)]. Initiate Sensipar treatment at a starting dose of 30 mg once daily.

2.5 Monitoring for Hypocalcemia

Once the maintenance dose has been established, serum calcium should be measured approximately monthly for patients with secondary hyperparathyroidism with CKD on dialysis, and every 2 months for patients with parathyroid carcinoma or primary hyperparathyroidism [see Dosage and Administration (2.2, 2.3)].

For secondary hyperparathyroidism patients with CKD on dialysis, if serum calcium falls below 8.4 mg/dL but remains above 7.5 mg/dL, or if symptoms of hypocalcemia occur, calcium-containing phosphate binders and/or vitamin D sterols can be used to raise serum calcium. If serum calcium falls below 7.5 mg/dL, or if symptoms of hypocalcemia persist and the dose of vitamin D cannot be increased, withhold administration of Sensipar until serum calcium levels reach 8.0 mg/dL and/or symptoms of hypocalcemia have resolved. Treatment should be reinitiated using the next lowest dose of Sensipar [see Dosage and Administration (2.2)].

3 DOSAGE FORMS AND STRENGTHS

Sensipar is available as film-coated tablets.

Sensipar tablets are formulated as light-green, film-coated, oval-shaped tablets marked with “AMG” on one side and “30” or “60” or “90” on the opposite side of the 30 mg, 60 mg, or 90 mg strengths, respectively.

4 CONTRAINDICATIONS

Sensipar treatment initiation is contraindicated if serum calcium is less than the lower limit of the normal range [see Warnings and Precautions (5.1)].

5 WARNINGS AND PRECAUTIONS

5.1 Hypocalcemia

Sensipar lowers serum calcium and can lead to hypocalcemia [see Adverse Reactions (6.1)]. Significant lowering of serum calcium can cause paresthesias, myalgias, muscle spasms, tetany, seizures, QT interval prolongation and ventricular arrhythmia. Life threatening events and fatal outcomes associated with hypocalcemia have been reported in patients treated with Sensipar, including in pediatric patients. The safety and effectiveness of Sensipar have not been established in pediatric patients [see Pediatric Use (8.4)].

Sensipar is not indicated for patients with CKD not on dialysis [see Indications and Usage (1)]. In patients with secondary HPT and CKD not on dialysis, the long-term safety and efficacy of Sensipar have not been established. Clinical studies indicate that Sensipar-treated patients with CKD not on dialysis have an increased risk for hypocalcemia compared with Sensipar-treated patients with CKD on dialysis, which may be due to lower baseline calcium levels. In a phase 3 study of 32 weeks duration and including 404 patients with CKD not on dialysis (302 cinacalcet, 102 placebo), in which the median dose for cinacalcet was 60 mg per day at the completion of the study, 80% of Sensipar-treated patients experienced at least one serum calcium value < 8.4 mg/dL compared with 5% of patients receiving placebo.

QT Interval Prolongation and Ventricular Arrhythmia

Decreases in serum calcium can also prolong the QT interval, potentially resulting in ventricular arrhythmia. Cases of QT prolongation and ventricular arrhythmia have been reported in patients treated with Sensipar. Patients with congenital long QT syndrome, history of QT interval prolongation, family history of long QT syndrome or sudden cardiac death, and other conditions that predispose to QT interval prolongation and ventricular arrhythmia may be at increased risk for QT interval prolongation and ventricular arrhythmias if they develop hypocalcemia due to Sensipar. Closely monitor corrected serum calcium and QT interval in patients at risk receiving Sensipar.

Seizures

In clinical studies, seizures (primarily generalized or tonic-clonic) were observed in 1.4% (43/3049) of Sensipar-treated patients and 0.7% (5/687) of placebo-treated patients. While the basis for the reported difference in seizure rate is not clear, the threshold for seizures is lowered by significant reductions in serum calcium levels. Monitor serum calcium levels in patients with seizure disorders receiving Sensipar.

Concurrent Administration with Other Calcium-Lowering Drug Products

Concurrent administration of Sensipar with calcium-lowering drugs including other calcium-sensing receptor agonists could result in severe hypocalcemia. Closely monitor serum calcium in patients receiving Sensipar and concomitant therapies known to lower serum calcium levels.

Patient Education and Hypocalcemia Treatment

Educate patients on the symptoms of hypocalcemia and advise them to contact a healthcare provider if they occur. If corrected serum calcium falls below the lower limit of normal or symptoms of hypocalcemia develop, start or increase calcium supplementation (including calcium, calcium-containing phosphate binders, and/or vitamin D sterols or increases in dialysate calcium concentration). Sensipar dose reduction or discontinuation of Sensipar may be necessary [see Dosage and Administration (2.2)].

5.2 Upper Gastrointestinal Bleeding

Cases of gastrointestinal bleeding, mostly upper gastrointestinal bleeding, have occurred in patients using calcimimetics, including Sensipar, from postmarketing and clinical trial sources. The exact cause of GI bleeding in these patients is unknown.

Patients with risk factors for upper GI bleeding (such as known gastritis, esophagitis, ulcers or severe vomiting) may be at increased risk for GI bleeding when receiving Sensipar treatment. Monitor patients for worsening of common GI adverse reactions of nausea and vomiting associated with Sensipar [see Adverse Reactions (6.1)] and for signs and symptoms of GI bleeding and ulcerations during Sensipar therapy. Promptly evaluate and treat any suspected GI bleeding.

5.3 Hypotension, Worsening Heart Failure and/or Arrhythmias

In postmarketing safety surveillance, isolated, idiosyncratic cases of hypotension, worsening heart failure, and/or arrhythmia have been reported in patients with impaired cardiac function, in which a causal relationship to Sensipar could not be completely excluded and which may be mediated by reductions in serum calcium levels [see Adverse Reactions (6.2)].

5.4 Adynamic Bone Disease

Adynamic bone disease may develop if iPTH levels are suppressed below 100 pg/mL. One clinical study evaluated bone histomorphometry in patients treated with Sensipar for 1 year. Three patients with mild hyperparathyroid bone disease at the beginning of the study developed adynamic bone disease during treatment with Sensipar. Two of these patients had iPTH levels below 100 pg/mL at multiple time points during the study. In three 6-month, phase 3 studies conducted in patients with CKD on dialysis, 11% of patients treated with Sensipar had mean iPTH values below 100 pg/mL during the efficacy-assessment phase. If iPTH levels decrease below 150 pg/mL in patients treated with Sensipar, the dose of Sensipar and/or vitamin D sterols should be reduced or therapy discontinued.

6 ADVERSE REACTIONS

The following adverse reactions are discussed in greater detail in other sections of labeling:

- Hypocalcemia [see Warnings and Precautions (5.1)]
- Upper Gastrointestinal Bleeding [see Warnings and Precautions (5.2)]
- Hypotension, Worsening Heart Failure and/or Arrhythmias [see Warnings and Precautions (5.3)]
- Adynamic Bone Disease [see Warnings and Precautions (5.4)]

6.1 Clinical Trials Experience

Because clinical trials are conducted under widely varying conditions, adverse reaction rates observed in the clinical trials of a drug cannot be directly compared with rates in the clinical trials of another drug and may not reflect the rates observed in clinical practice.

Secondary Hyperparathyroidism in Patients with Chronic Kidney Disease on Dialysis

In three double-blind, placebo-controlled clinical trials, 1126 patients with CKD on dialysis received study drug (656 Sensipar, 470 placebo) for up to 6 months. The most frequently reported adverse reactions are listed in Table 1.

Seizures were observed in 1.4% (13/910) of Sensipar-treated patients and 0.7% (5/641) of placebo-treated patients across all completed placebo-controlled trials.

Table 1. Adverse Reactions with Frequency ≥ 5% in Patients on Dialysis in Short-Term Studies for up to 6 Months
 |  | Placebo | Sensipar
 |  | (n = 470) | (n = 656)
Event*: |  | (%) | (%)
Nausea |  | 19 | 31
Vomiting |  | 15 | 27
Diarrhea |  | 20 | 21
Myalgia |  | 14 | 15
Dizziness |  | 8 | 10
Hypertension |  | 5 | 7
Asthenia |  | 4 | 7
Anorexia |  | 4 | 6
Pain Chest, Non-Cardiac |  | 4 | 6
Dialysis Access Site Infection |  | 4 | 5
*Included are events that were reported at a greater incidence in the Sensipar group than in the placebo group.

In a randomized, double-blind placebo-controlled study of 3883 patients with secondary HPT and CKD receiving dialysis in which patients were treated for up to 64 months (mean duration of treatment was 21 months in the Sensipar group), the most frequently reported adverse reactions (incidence of ≥ 5% in the Sensipar group and a difference ≥ 1% compared to placebo) are listed in Table 2.

Table 2. Frequency of Adverse Reactions in Dialysis Patients Treated for up to 64 Months in a Long-Term Study^1
 | Placebo (n = 1923) | Sensipar (n = 1938)
 | 3699 subject-years | 4044 subject-years
Percent of subjects reporting | 90.9 | 93.2
Adverse Reactions (%)
Nausea | 15.5 | 29.1
Vomiting | 13.7 | 25.6
Diarrhea | 18.7 | 20.5
Dyspnea | 11.5 | 13.4
Cough | 9.8 | 11.7
Hypotension | 10.5 | 11.6
Headache | 9.6 | 11.5
Hypocalcemia | 1.4 | 11.2
Muscle spasms | 9.2 | 11.1
Abdominal pain | 9.6 | 10.9
Abdominal pain upper | 6.3 | 8.2
Hyperkalemia | 6.1 | 8.1
Upper respiratory tract infection | 6.3 | 7.6
Dyspepsia | 4.6 | 7.4
Dizziness | 4.7 | 7.3
Decreased appetite | 3.5 | 5.9
Asthenia | 3.8 | 5.4
Constipation | 3.8 | 5.0
^1 Adverse reactions that occurred in ≥ 5% frequency in the Sensipar group and a difference ≥ 1% compared to the placebo group (Safety Analysis Set).
Crude incidence rate = 100 * Total number of subjects with event/ n
n = Number of subjects receiving at least one dose of study drug.

Additional adverse reaction rates from the long-term, randomized, double-blind placebo-controlled study for Sensipar versus placebo are as follows: seizure (2.5%, 1.6%), rash (2.2%, 1.9%), hypersensitivity reactions (9.4%, 8.3%).

Patients with Parathyroid Carcinoma and Primary Hyperparathyroidism

The safety profile of Sensipar in these patient populations is generally consistent with that seen in patients with CKD on dialysis. Forty six patients were treated with Sensipar in a single-arm study, 29 with Parathyroid Carcinoma and 17 with intractable pHPT. Nine (20%) of the patients withdrew from the study due to adverse events. The most frequent adverse reactions and the most frequent cause of withdrawal in these patient populations were nausea and vomiting. Severe or prolonged cases of nausea and vomiting can lead to dehydration and worsening hypercalcemia so careful monitoring of electrolytes is recommended in patients with these symptoms.

Eight patients died during treatment with Sensipar in this study, 7 with Parathyroid Carcinoma (24%) and 1 (6%) with intractable pHPT. Causes of death were cardiovascular (5 patients), multi-organ failure (1 patient), gastrointestinal hemorrhage (1 patient) and metastatic carcinoma (1 patient). Adverse events of hypocalcemia were reported in three patients (7%).

Seizures were observed in 0.7% (1/140) of cinacalcet-treated patients and 0.0% (0/46) of placebo-treated patients in all clinical studies.

Table 3. Adverse Reactions with Frequency ≥ 10% in a Single-Arm, Open-Label Study in Patients with Primary Hyperparathyroidism or Parathyroid Carcinoma
 | Sensipar
 | Parathyroid Carcinoma (n = 29) |  | Intractable pHPT (n = 17) | Total (n = 46)
 | n (%) | n (%) |  | n (%)
Number of Subjects Reporting Adverse | 28 (97) | 17 (100) |  | 45 (98)
Reactions
Nausea | 19 (66) | 10 (59) |  | 29 (63)
Vomiting | 15 (52) | 6 (35) |  | 21 (46)
Paresthesia | 4 (14) | 5 (29) |  | 9 (20)
Fatigue | 6 (21) | 2 (12) |  | 8 (17)
Fracture | 6 (21) | 2 (12) |  | 8 (17)
Hypercalcemia | 6 (21) | 2 (12) |  | 8 (17)
Anorexia | 6 (21) | 1 (6) |  | 7 (15)
Asthenia | 5 (17) | 2 (12) |  | 7 (15)
Dehydration | 7 (24) | 0 (0) |  | 7 (15)
Anemia | 5 (17) | 1 (6) |  | 6 (13)
Arthralgia | 5 (17) | 1 (6) |  | 6 (13)
Constipation | 3 (10) | 3 (18) |  | 6 (13)
Depression | 3 (10) | 3 (18) |  | 6 (13)
Headache | 6 (21) | 0 (0) |  | 6 (13)
Infection Upper Respiratory | 3 (10) | 2 (12) |  | 5 (11)
Pain Limb | 3 (10) | 2 (12) |  | 5 (11)
n = Number of subjects receiving at least one dose of study drug.
pHPT = primary hyperparathyroidism.

In a randomized double-blind, placebo-controlled study of 67 patients with primary hyperparathyroidism for whom parathyroidectomy would be indicated on the basis of serum calcium levels, but who are unable to undergo surgery, the most common adverse reactions are listed in Table 4.

Table 4. Adverse Reactions Occurring in ≥ 10% of Subjects in a Double-Blind, Placebo-Controlled Study in Patients with Primary Hyperparathyroidism

Adverse Reaction | Placebo (n = 34) n (%) | Cinacalcet (n = 33) n (%)
Nausea | 6 (18) | 10 (30)
Muscle spasms | 0 (0) | 6 (18)
Headache | 2 (6) | 4 (12)
Back pain | 2 (6) | 4 (12)
n = Number of subjects receiving at least one dose of study drug Coded using MedDRA version 16.0.

Hypocalcemia

In 26-week studies of patients with secondary HPT and CKD on dialysis 66% of patients receiving Sensipar compared with 25% of patients receiving placebo developed at least one serum calcium value less than 8.4 mg/dL, whereas, 29% of patients receiving Sensipar compared with 11% of patients receiving placebo developed at least one serum calcium value less than 7.5 mg/dL. Less than 1% of patients in each group permanently discontinued study drug due to hypocalcemia.

In a randomized, double-blind, placebo-controlled study in patients with secondary HPT and CKD receiving dialysis in which patients were treated for up to 64 months (mean duration of treatment was 21 months in the cinacalcet group), 75% of patients receiving Sensipar compared with 29% of patients receiving placebo developed at least one serum calcium value less than 8.4 mg/dL and 33% of cinacalcet patients compared with 12% of patients receiving placebo had at least one serum calcium value less than 7.5 mg/dL. Most of the cases of severe hypocalcemia less than 7.5 mg/dL (21/33 = 64%) occurred during the first 6 months. In this trial, 1.1% of patients receiving Sensipar and 0.1% of patients receiving placebo permanently discontinued study drug due to hypocalcemia.

During a placebo-controlled part of a 52-week study in patients with primary HPT who met criteria for parathyroidectomy on the basis of corrected total serum calcium (> 11.3 mg/dL [2.82 mmol/L] and ≤ 12.5 mg/dL [3.12 mmol/L]), serum calcium less than 8.4 mg/dL was observed in 6.1% (2/33) of Sensipar-treated patients and 0% (0/34) of placebo-treated patients.

6.2 Postmarketing Experience

The following adverse reactions have been identified during post approval use of Sensipar. Because these reactions are reported voluntarily from a population of uncertain size, it is not always possible to reliably estimate their frequency or establish a causal relationship to drug exposure.

- Rash and hypersensitivity reactions (including angioedema and urticaria), and myalgia
- Isolated, idiosyncratic cases of hypotension, worsening heart failure, and/or arrhythmia have been reported in patients with impaired cardiac function
- Gastrointestinal bleeding
- Chondrocalcinosis pyrophosphate (acute pseudogout)

7 DRUG INTERACTIONS

7.1 Strong CYP3A4 Inhibitors

Cinacalcet is partially metabolized by CYP3A4. Dose adjustment of Sensipar may be required if a patient initiates or discontinues therapy with a strong CYP3A4 inhibitor (e.g., ketoconazole, itraconazole). The iPTH and serum calcium concentrations should be closely monitored in these patients [see Clinical Pharmacology (12.3)].

7.2 CYP2D6 Substrates

Cinacalcet is a strong inhibitor of CYP2D6. Dose adjustments may be required for concomitant medications that are predominantly metabolized by CYP2D6 (e.g., desipramine, metoprolol, and carvedilol) and particularly those with a narrow therapeutic index (e.g., flecainide and most tricyclic antidepressants) [see Clinical Pharmacology (12.3)].

8 USE IN SPECIFIC POPULATIONS

8.1 Pregnancy

Risk Summary

Limited case reports of Sensipar use in pregnant women are insufficient to inform a drug associated risk of adverse developmental outcomes. In animal reproduction studies, when female rats were exposed to cinacalcet during the period of organogenesis through to weaning at 2-3 times the systemic drug levels (based on AUC) at the maximum recommended human dose (MRHD) of 180 mg/day, peripartum and early postnatal pup loss and reduced pup body weight gain were observed in the presence of maternal hypocalcemia [see Data].

The estimated background risk of major birth defects and miscarriage for the indicated populations is unknown. In the U.S. general population, the estimated background risk of major birth defects and miscarriage in clinically recognized pregnancies is 2-4% and 15-20%, respectively.

Data

Animal Data

In pregnant female rats given oral gavage doses of 2, 25, 50 mg/kg/day cinacalcet during gestation, no teratogenicity was observed at doses up to 50 mg/kg/day (exposure 4 times those resulting with a human oral dose of 180 mg/day based on AUC comparison). Decreased fetal body weights were observed at all doses (less than 1 to 4 times a human oral dose of 180 mg/day based on AUC comparison) in conjunction with maternal toxicity (decreased food consumption and body weight gain).

In pregnant female rabbits given oral gavage doses of 2, 12, 25 mg/kg/day cinacalcet during gestation, no adverse fetal effects were observed (exposures less than with a human oral dose of 180 mg/day based on AUC comparisons). Reductions in maternal food consumption and body weight gain were seen at doses of 12 and 25 mg/kg/day. Cinacalcet has been shown to cross the placental barrier in rabbits.

In pregnant rats given oral gavage doses of 5, 15, 25 mg/kg/day cinacalcet during gestation through lactation, no adverse fetal or pup (post-weaning) effects were observed at 5 mg/kg/day (exposures less than with a human therapeutic dose of 180 mg/day based on AUC comparisons). Higher doses of 15 and 25 mg/kg/day cinacalcet (exposures 2 to 3 times a human oral dose of 180 mg/day based on AUC comparisons) were accompanied by maternal signs of hypocalcemia (periparturient mortality and early postnatal pup loss), and reductions in postnatal maternal and pup body weight gain.

8.2 Lactation

Risk Summary

There are no data regarding the presence of Sensipar in human milk or effects on the breastfed infant or on milk production. Studies in rats showed that cinacalcet was excreted in the milk. The developmental and health benefits of breastfeeding should be considered along with the mother’s clinical need for Sensipar and any potential adverse effects on the breastfed infant from Sensipar or from the underlying maternal condition.

8.4 Pediatric Use

The safety and efficacy of Sensipar have not been established in pediatric patients.

The use of Sensipar for the treatment of secondary HPT in pediatric patients with CKD on dialysis was evaluated in two randomized, controlled studies (Pediatric Study 1 and Study 2) where 47 pediatric patients aged 6 years to less than 18 years received at least one dose of Sensipar and in one single-arm study (Pediatric Study 3) where 17 pediatric patients aged 28 days to less than 6 years received at least one dose of Sensipar. Dosing with Sensipar in Pediatric Study 1 was stopped because of a fatality in a Sensipar-treated individual. The individual was noted to be severely hypocalcemic at the time of death. The cause of death was multifactorial and a contribution of Sensipar to the death could not be excluded [see Warnings and Precautions (5.1)]. Study 1 was terminated and changes to Sensipar dosing after the fatality were implemented in Pediatric Study 2 and Study 3 to minimize the risk of severe hypocalcemia. The data in Pediatric Studies 2 and 3 were insufficient to establish the safety and efficacy of Sensipar for the treatment of secondary HPT in pediatric patients with CKD on dialysis. In aggregate, the pediatric studies did not establish a safe and effective Sensipar dosing regimen for the pediatric population.

8.5 Geriatric Use

Of the total number of subjects (n = 1136) in clinical studies of Sensipar, 26 percent were 65 and over, and 9 percent were 75 and over. No overall differences in the safety or effectiveness were observed between these subjects and younger subjects, and other reported clinical experience has not identified differences in responses between the elderly and younger subjects, but greater sensitivity of some older individuals cannot be ruled out [see Clinical Studies (14) and Clinical Pharmacology (12.3)].

8.6 Renal Impairment

No dosage adjustment is necessary for renal impairment [see Clinical Pharmacology (12.3)].

8.7 Hepatic Impairment

Patients with moderate and severe hepatic impairment should have serum calcium, serum phosphorus, and iPTH levels monitored closely throughout treatment with Sensipar because cinacalcet exposure (AUC0-infinite) is increased by 2.4 and 4.2 fold, respectively, in these patients [see Clinical Pharmacology (12.3)].

10 OVERDOSAGE

Overdosage of Sensipar may lead to hypocalcemia. In the event of overdosage, patients should be monitored for signs and symptoms of hypocalcemia and appropriate measures taken to correct serum calcium levels [see Warnings and Precautions (5.1)].

Since Sensipar is highly protein bound, hemodialysis is not an effective treatment for overdosage of Sensipar.

11 DESCRIPTION

Sensipar tablets contain the hydrochloride salt of the active ingredient cinacalcet, a positive modulator of the calcium sensing receptor . The empirical formula for cinacalcet is C22H22F3N•HCl with a molecular weight of 393.9 g/mol (hydrochloride salt) and 357.4 g/mol (free base). It has one chiral center having an R-absolute configuration. The R-enantiomer is the more potent enantiomer and has been shown to be responsible for pharmacodynamic activity. The hydrochloride salt of cinacalcet is a white to off-white, crystalline solid that is soluble in methanol or 95% ethanol and slightly soluble in water. The hydrochloride salt of cinacalcet is described chemically as N-[1-(R)-(-)-(1-naphthyl)ethyl]-3-[3-(trifluoromethyl)phenyl]-1-aminopropane hydrochloride and has the following structural formula:

Sensipar tablets are formulated as light-green, film-coated, oval-shaped tablets for oral administration in strengths of 30 mg, 60 mg, and 90 mg of cinacalcet as the free base equivalent (33 mg, 66 mg, and 99 mg as the hydrochloride salt, respectively).

Inactive Ingredients

The following are the inactive ingredients in Sensipar tablets: pre-gelatinized starch, microcrystalline cellulose, povidone, crospovidone, colloidal silicon dioxide and magnesium stearate. Tablets are coated with color (Opadry® II green), clear film coat (Opadry® clear), and carnauba wax.

12 CLINICAL PHARMACOLOGY

12.1 Mechanism of Action

The calcium-sensing receptor on the surface of the chief cell of the parathyroid gland is the principal regulator of PTH synthesis and secretion. Cinacalcet, the active ingredient in Sensipar, is a calcimimetic agent that directly lowers PTH levels by increasing the sensitivity of the calcium-sensing receptor to activation by extracellular calcium. The reduction in PTH is associated with a concomitant decrease in serum calcium levels.

12.2 Pharmacodynamics

Reduction in iPTH levels correlated with the plasma cinacalcet concentrations in patients with CKD. The nadir in iPTH level occurs approximately 2 to 6 hours post dose, corresponding with the maximum plasma concentration (Cmax) of cinacalcet. After steady-state cinacalcet concentrations are reached (which occurs within 7 days of dose change), serum calcium concentrations remain constant over the dosing interval in patients with CKD.

Reductions in PTH are associated with a decrease in bone turnover and bone fibrosis in patients with CKD on dialysis and uncontrolled secondary HPT.

12.3 Pharmacokinetics

Absorption and Distribution

After oral administration of cinacalcet, Cmax is achieved in approximately 2 to 6 hours. Cinacalcet Cmax and AUC(0-infinite) were increased by 82% and 68%, respectively, following administration with a high-fat meal compared with fasting in healthy volunteers. The Cmax and AUC(0-infinite) of cinacalcet were increased by 65% and 50%, respectively, when cinacalcet was administered with a low-fat meal compared with fasting.

After absorption, cinacalcet concentrations decline in a biphasic fashion with an initial half-life of approximately 6 hours and terminal half-life of 30 to 40 hours. Steady-state drug levels are achieved within 7 days, and the mean accumulation ratio is approximately 2 with once daily oral administration. The median accumulation ratio is approximately 2 to 5 with twice daily oral administration. The AUC and Cmax of cinacalcet increase proportionally over the dose range of 30 to 180 mg once daily. The pharmacokinetic profile of cinacalcet does not change over time with once daily dosing of 30 to 180 mg. The volume of distribution is approximately 1000 L, indicating extensive distribution. Cinacalcet is approximately 93% to 97% bound to plasma protein(s). The ratio of blood cinacalcet concentration to plasma cinacalcet concentration is 0.80 at a blood cinacalcet concentration of 10 ng/mL.

Metabolism and Excretion

Cinacalcet is metabolized by multiple enzymes, primarily CYP3A4, CYP2D6, and CYP1A2. After administration of a 75 mg radiolabeled dose to healthy volunteers, cinacalcet was metabolized via: 1) oxidative N-dealkylation to hydrocinnamic acid and hydroxy-hydrocinnamic acid, which are further metabolized via β-oxidation and glycine conjugation; the oxidative N-dealkylation process also generates metabolites that contain the naphthalene ring; and 2) oxidation of the naphthalene ring on the parent drug forming dihydrodiols, which are further conjugated with glucuronic acid. The plasma concentrations of the major circulating metabolites, including the cinnamic acid derivatives and glucuronidated dihydrodiols, markedly exceed the parent drug concentrations. The hydrocinnamic acid metabolite and glucuronide conjugates have minimal or no calcimimetic activity. Renal excretion of metabolites was the primary route of elimination of radioactivity. Approximately 80% of the dose was recovered in the urine and 15% in the feces.

Specific Populations

Age: Geriatric Population

The pharmacokinetic profile of cinacalcet in geriatric patients (age ≥ 65 years, n = 12) is similar to that for patients who are < 65 years of age (n = 268) [see Use in Specific Populations (8.5)].

Hepatic Impairment

The disposition of a 50 mg Sensipar single dose was compared between patients with hepatic impairment and patients with normal hepatic function. Cinacalcet exposure (AUC(0-infinite)) was comparable between healthy volunteers and patients with mild hepatic impairment. However, in patients with moderate and severe hepatic impairment (as indicated by the Child-Pugh method), cinacalcet exposures (AUC(0-infinite)) were 2.4 and 4.2 fold higher, respectively, than that in healthy volunteers. The mean half-life of cinacalcet increased from 49 hours in healthy volunteers to 65 hours and 84 hours in patients with moderate and severe hepatic impairment, respectively. Protein binding of cinacalcet is not affected by impaired hepatic function [see Use in Specific Populations (8.7)].

Renal Impairment

The pharmacokinetic profile of a 75 mg Sensipar single dose in patients with mild, moderate, and severe renal impairment, and those on hemodialysis or peritoneal dialysis is comparable with that in healthy volunteers [see Use in Specific Populations (8.6)].

Drug Interactions

In vitro studies indicate that cinacalcet is a strong inhibitor of CYP2D6, but not an inhibitor of CYP1A2, CYP2C9, CYP2C19, and CYP3A4. In vitro induction studies indicate that cinacalcet is not an inducer of CYP450 enzymes. Tables 5 and 6 list the findings from in vivo drug-drug interaction studies.

Table 5. Effect of co-administered drugs on cinacalcet
Co-administered drug and dosing regimen | Cinacalcet
 | Dose* | Mean change in AUC (0-inf) |  | Mean change in Cmax
200 mg ketoconazole twice daily for 7 days | 90 mg on day 5 | ↑127% | ↑116%
1500 mg calcium carbonate, single dose | 100 mg | ↓6% | ↓5%
80 mg pantoprazole daily for 3 days | 90 mg on day 3 | ↑1% | ↓3%
2400 mg sevelamer HCl three times a day for 2 days | 90 mg on day 1 with first dose of sevelamer | ↓4% | ↓7%
*Single dose.

Table 6. Effect of cinacalcet co-administration on other drugs
Cinacalcet dosing regimen | Co-administered drug
 | Name and Dose | Mean change in AUC (0-inf) | Mean change in Cmax
30 mg twice daily for 8 days | 25 mg warfarin* tablet† | ↑1% for R-warfarin ↓1% for S-warfarin | ↓10% for R-warfarin ↓12% for S-warfarin
90 mg daily for 7 days to CYP2D6 extensive metabolizers | 50 mg desipramine† | ↑264% | ↑75%
90 mg daily for 5 days | 2 mg midazolam† | ↑5% | ↓5%
25 or 100 mg single dose to CYP2D6 extensive metabolizers | 50 mg amitriptyline single dose | ↑21-22% for amitriptyline ↑17-23% for nortriptyline‡ | ↑13-21% for amitriptyline ↑11-15% for nortriptyline‡
*No significant change in prothrombin time.
†Single dose on day 5.
‡Nortriptyline is an active metabolite of amitriptyline.

13 NONCLINICAL TOXICOLOGY

13.1 Carcinogenesis, Mutagenesis, Impairment of Fertility

Carcinogenicity
Standard lifetime dietary carcinogenicity bioassays were conducted in mice and rats. Mice were given cinacalcet at dietary doses of 15, 50, and 125 mg/kg/day in males and 30, 70, and 200 mg/kg/day in females (exposures up to 2 times those resulting with a human oral dose of 180 mg/day based on AUC comparison). Rats were given dietary doses of 5, 15, and 35 mg/kg/day in males and 5, 20, and 35 mg/kg/day in females (exposures up to 2 times those resulting with a human oral dose of 180 mg/day based on AUC comparison). No increased incidence of tumors was observed following treatment with cinacalcet.

Mutagenicity
Cinacalcet was not genotoxic in the Ames bacterial mutagenicity assay, nor in the Chinese Hamster Ovary (CHO) cell HGPRT forward mutation assay and CHO cell chromosomal aberration assay, with and without metabolic activation, nor in the in vivo mouse micronucleus assay.

Impairment of Fertility
Female rats were given oral gavage doses of 5, 25, and 75 mg/kg/day cinacalcet beginning 2 weeks before mating and continuing through gestation day 7. Male rats were given oral doses 4 weeks prior to mating, during mating (3 weeks) and 2 weeks postmating. No effects were observed in male or female fertility at 5 and 25 mg/kg/day (exposures up to 3 times those resulting with a human oral dose of 180 mg/day based on AUC comparison). At 75 mg/kg/day, there were slight adverse effects (slight decreases in body weight and food consumption) in males and females.

14 CLINICAL STUDIES

14.1 Secondary Hyperparathyroidism in Patients with Chronic Kidney Disease on Dialysis

Three 6-month, multicenter, randomized, double-blind, placebo-controlled clinical studies of similar design were conducted in patients with CKD on dialysis. A total of 665 patients were randomized to Sensipar and 471 patients to placebo. The mean age of the patients was 54 years, 62% were male, and 52% were Caucasian. The average baseline iPTH level by the Nichols IRMA was 712 pg/mL, with 26% of the patients having a baseline iPTH level > 800 pg/mL. The mean baseline Ca x P product was 61 mg^2/dL^2. The average duration of dialysis prior to study enrollment was 67 months. Ninety-six percent of patients were on hemodialysis and 4% on peritoneal dialysis. At study entry, 66% of the patients were receiving vitamin D sterols and 93% were receiving phosphate binders. Sensipar (or placebo) was initiated at a dose of 30 mg once daily and titrated every 3 or 4 weeks to a maximum dose of 180 mg once daily to achieve an iPTH of ≤ 250 pg/mL. The dose was not increased if a patient had any of the following: iPTH ≤ 200 pg/mL, serum calcium < 7.8 mg/dL, or any symptoms of hypocalcemia. If a patient experienced symptoms of hypocalcemia or had a serum calcium < 8.4 mg/dL, calcium supplements and/or calcium-based phosphate binders could be increased. If these measures were insufficient, the vitamin D dose could be increased. Approximately 70% of patients in the Sensipar arm and 80% of the patients in the placebo arm completed the 6-month studies. In the primary efficacy analysis, 40% of the patients on Sensipar and 5% of placebo-treated patients achieved an iPTH ≤ 250 pg/mL (p < 0.001) (Table 7, Figure 1). These studies showed that Sensipar reduced iPTH while lowering Ca x P, calcium, and phosphorus levels (Table 7, Figure 2). The median dose of Sensipar at the completion of the studies was 90 mg. Patients with milder disease typically required lower doses.

Similar results were observed when either the iPTH or biointact PTH (biPTH) assay was used to measure PTH levels in CKD patients on dialysis; treatment with cinacalcet did not alter the relationship between iPTH and biPTH.

Table 7. Effects of Sensipar on iPTH, Ca x P, Serum Calcium, and Serum Phosphorus in 6-month Phase 3 Studies (Patients on Dialysis)
 |  |  |  | Study 1 |  | Study 2 |  | Study 3
 |  |  |  | Placebo | Sensipar | Placebo | Sensipar | Placebo | Sensipar
 |  |  |  | (n = 205) | (n = 205) | (n = 165) | (n = 166) | (n = 101) | (n = 294)
iPTH
 |  | Baseline (pg/mL): Median Mean (SD) |  | 535 651 (398) | 537 636 (341) | 556 630 (317) | 547 652 (372) | 670 832 (486) | 703 848 (685)
 |  | Evaluation Phase (pg/mL) |  | 563 | 275 | 592 | 238 | 737 | 339
 |  | Median Percent Change |  | +3.8 | -48.3 | +8.4 | -54.1 | +2.3 | -48.2
 |  | Patients Achieving Primary Endpoint (iPTH ≤ 250 pg/mL) (%)a |  | 4% | 41%** | 7% | 46%** | 6% | 35%**
 |  | Patients Achieving ≥ 30% Reduction in iPTH (%)a |  | 11% | 61% | 12% | 68% | 10% | 59%
 |  | Patients Achieving iPTH ≤ 250 pg/mL and Ca x P < 55 mg^2/dL^2 (%) |  | 1% | 32% | 5% | 35% | 5% | 28%
Ca x P
 |  | Baseline (mg^2/dL^2) |  | 62 | 61 | 61 | 61 | 61 | 59
 |  | Evaluation Phase (mg^2/dL^2) |  | 59 | 52 | 59 | 47 | 57 | 48
 |  | Median Percent Change |  | -2.0 | -14.9 | -3.1 | -19.7 | -4.8 | -15.7
Calcium
 | Baseline (mg/dL) |  |  | 9.8 | 9.8 | 9.9 | 10.0 | 9.9 | 9.8
 | Evaluation Phase (mg/dL) |  |  | 9.9 | 9.1 | 9.9 | 9.1 | 10.0 | 9.1
 | Median Percent Change |  |  | +0.5 | -5.5 | +0.1 | -7.4 | +0.3 | -6.0
Phosphorus
 | Baseline (mg/dL) |  |  | 6.3 | 6.1 | 6.1 | 6.0 | 6.1 | 6.0
 | Evaluation Phase (mg/dL) |  |  | 6.0 | 5.6 | 5.9 | 5.1 | 5.6 | 5.3
 | Median Percent Change |  |  | -1.0 | -9.0 | -2.4 | -12.4 | -5.6 | -8.6
** p < 0.001 compared with placebo; p-values presented for primary endpoint only.
a iPTH value based on averaging over the evaluation phase (defined as weeks 13 to 26 in studies 1 and 2 and weeks 17 to 26 in study 3).
Values shown are medians unless indicated otherwise.

Figure 1. Mean (SE) iPTH Values (Pooled Phase 3 Studies)

Data are presented for patients who completed the studies; Placebo (n = 342), Sensipar (n = 439).

Figure 2. Mean (SE) Ca x P Values (Pooled Phase 3 Studies)

Data are presented for patients who completed the studies; Placebo (n = 342), Sensipar (n = 439).

Reductions in iPTH and Ca x P were maintained for up to 12 months of treatment.

Sensipar decreased iPTH and Ca x P levels regardless of disease severity (i.e., baseline iPTH value), duration of dialysis, and whether or not vitamin D sterols were administered. Approximately 60% of patients with mild (iPTH ≥ 300 to ≤ 500 pg/mL), 41% with moderate (iPTH > 500 to 800 pg/mL), and 11% with severe (iPTH > 800 pg/mL) secondary HPT achieved a mean iPTH value of ≤ 250 pg/mL. Plasma iPTH levels were measured using the Nichols IRMA.

14.2 Parathyroid Carcinoma

Twenty-nine patients with Parathyroid Carcinoma were enrolled in a single-arm, open-label study. The study consisted of two phases, a dose-titration phase and a maintenance phase. Patients initially received 30 mg cinacalcet twice daily and then were titrated every 2 weeks to a maximum dose of 90 mg four times daily. Dosage escalation during the variable-length (2 to 16 weeks) titration phase continued until the serum calcium concentration was ≤ 10 mg/dL (2.5 mmol/L), the patient reached the highest possible dosage, or adverse events precluded further dosage increases.

Twenty-nine patients entered the study. The median exposure to cinacalcet was 229 days (range: 1 to 1051). At baseline the mean (SE) serum calcium was 14.1 (0.4) mg/dL. At the end of the titration phase, the mean (SE) serum calcium was 12.4 (0.5) mg/dL, which is a mean reduction of 1.7 (0.6) mg/dL from baseline. Figure 3 illustrates mean serum calcium (mg/dL) over time for all patients still on study at each time point from the beginning of titration to study visit week 80. Daily dose during the study ranged from 30 mg twice daily to 90 mg four times daily.

Figure 3. Serum Calcium Values in Patients with Parathyroid Carcinoma Receiving Sensipar at Baseline, Titration, and Maintenance Phase

n = Number of patients with non-missing values at the timepoint.
End of Titration (EOT) phase could occur at any visit from week 2 to 16. Patients at EOT are those who completed titration.

14.3 Patients with Hypercalcemia Due to Primary Hyperparathyroidism

Seventeen patients with severe hypercalcemia due to primary HPT, who had failed or had contraindications to parathyroidectomy, participated in an open-label, single-arm study. The study consisted of two phases, a dose-titration phase and a maintenance phase. In this trial, severe hypercalcemia was defined as a screening serum calcium level of > 12.5 mg/dL. Patients initially received 30 mg cinacalcet twice daily and then were titrated every 2 weeks to a maximum dose of 90 mg 4 times daily. Dosage escalation during the variable-length (2 to 16 weeks) titration phase continued until the serum calcium concentration was ≤ 10 mg/dL (2.5 mmol/L), the patient reached the highest possible dosage, or adverse events precluded further dosage increases.

Seventeen patients entered the study. The median exposure to cinacalcet was 270 days (range: 32 to 1,105). At baseline the mean (SE) serum calcium was 12.7 (0.2) mg/dL. At the end of the titration phase the mean (SE) serum calcium was 10.4 (0.3) mg/dL, which is a mean reduction of 2.3 (0.3) mg/dL from baseline. Figure 4 illustrates mean serum calcium (mg/dL) over time for all patients still on study at each time point from the beginning of titration to study visit week 80. Daily dose during the study ranged from 30 mg twice a day to 90 mg four times a day.

Figure 4. Mean Serum Calcium (SE) at Baseline, End of Titration, and Scheduled Maintenance Visits (Patients with Severe intractable primary HPT)

n = Number of patients with non-missing values at the timepoint.
End of Titration (EOT) phase could occur at any visit from week 2 to 16. Patients at EOT are those who completed titration.

Sixty-seven patients with primary HPT who met criteria for parathyroidectomy on the basis of corrected total serum calcium (> 11.3 mg/dL [2.82 mmol/L] and ≤ 12.5 mg/dL [3.12 mmol/L]), but who were unable to undergo parathyroidectomy participated in a randomized, double-blind, placebo-controlled study. A total of 33 patients were randomized to Sensipar and 34 patients randomized to placebo. The mean age of the patients was 72 years, 52% were female, 61% were Caucasian, and 5% were Blacks. The study started with a 12-week titration phase, followed by a 16-week efficacy-assessment phase. Cinacalcet was initiated at a dose of 30 mg twice daily and titrated to maintain a corrected total serum calcium concentration within the normal range. During the efficacy period a significantly higher percentage of cinacalcet-treated patients compared with the placebo-treated patients achieved mean corrected total serum calcium concentration (≤ 10.3 mg/dL [2.57 mmol/L], 75.8% vs 0%, p < 0.001) and ≥ 1 mg/dL [0.25 mmol/L] decrease from baseline in mean corrected total serum calcium concentration (84.8% vs 5.9%, p < 0.001). The median dose of Sensipar at the completion of the study was 60 mg/day.

16 HOW SUPPLIED/STORAGE AND HANDLING

Sensipar 30 mg tablets are formulated as light-green, film-coated, oval-shaped tablets marked with “AMG” on one side and “30” on the opposite side, packaged in bottles of 30 tablets. (NDC 55513-073-30)

Sensipar 60 mg tablets are formulated as light-green, film-coated, oval-shaped tablets marked with “AMG” on one side and “60” on the opposite side, packaged in bottles of 30 tablets. (NDC 55513-074-30)

Sensipar 90 mg tablets are formulated as light-green, film-coated, oval-shaped tablets marked with “AMG” on one side and “90” on the opposite side, packaged in bottles of 30 tablets. (NDC 55513-075-30)

Storage

Store at 25°C (77°F); excursions permitted from 15°C to 30°C (59°F to 86°F). [See USP controlled room temperature].

17 PATIENT COUNSELING INFORMATION

- Hypocalcemia: Advise patients to report symptoms of hypocalcemia, including paresthesias, myalgias, muscle spasms, and seizures, to their healthcare provider [see Warnings and Precautions (5.1)].
- Upper Gastrointestinal Bleeding: Advise patients to report any symptoms of upper gastrointestinal bleeding to their health care provider [see Warnings and Precautions (5.2)].
- Heart Failure: Advise patients with heart failure that use of Sensipar may worsen their heart failure and additional monitoring may be required [see Warnings and Precautions (5.3)].
- Advise patients to report nausea and vomiting to their health care provider [see Adverse Reactions (6.1)].
- Advise patients to take Sensipar with food or shortly after a meal and to take the tablets whole and not divide them [see Dosage and Administration (2.1)].
- Inform patients of the importance of regular blood tests, in order to monitor the safety and efficacy of Sensipar therapy.

Sensipar® (cinacalcet) Tablets

Manufactured by:
Amgen Inc.
One Amgen Center Drive
Thousand Oaks, California 91320-1799

Patent: http://pat.amgen.com/sensipar/

© 2004-2019 Amgen Inc. All rights reserved.

www.sensipar.com

1-800-77-AMGEN (1-800-772-6436)

1xxxxxx – v14

PRINCIPAL DISPLAY PANEL

AMGEN®

NDC 55513-073-30

Sensipar®

(cinacalcet) Tablets

Rx Only

30 tablets

30 mg

Each tablet contains:

Cinacalcet 30 mg (equivalent to 33 mg of cinacalcet hydrochloride).

Store at 25°C (77°F); excursions permitted to 15-30°C (59-86°F).

See USP controlled room temperature.

Dispense in tight, light-resistant container per USP.

Dosage : See Package Insert.

© 2004-2018 Amgen Inc. All rights reserved.

Patent : http://pat.amgen.com/sensipar/

Distributed by : Amgen,

One Amgen Center Drive,

Thousand Oaks, CA 91320-1799

Made in Japan

PRINCIPAL DISPLAY PANEL

AMGEN®

NDC 55513-074-30

Sensipar®

(cinacalcet) Tablets

Rx Only

30 tablets

60 mg

Each tablet contains:

Cinacalcet 60 mg (equivalent to 66 mg of cinacalcet hydrochloride).

Store at 25°C (77°F); excursions permitted to 15-30°C (59-86°F).

See USP controlled room temperature.

Dispense in tight, light-resistant container per USP.

Dosage : See Package Insert.

© 2004-2018 Amgen Inc. All rights reserved.

Patent : http://pat.amgen.com/sensipar/

Distributed by : Amgen,

One Amgen Center Drive,

Thousand Oaks, CA 91320-1799

Made in Japan

PRINCIPAL DISPLAY PANEL

AMGEN®

NDC 55513-075-30

Sensipar®

(cinacalcet) Tablets

Rx Only

30 tablets

90 mg

Each tablet contains:

Cinacalcet 90 mg (equivalent to 99 mg of cinacalcet hydrochloride).

Store at 25°C (77°F); excursions permitted to 15-30°C (59-86°F).

See USP controlled room temperature.

Dispense in tight, light-resistant container per USP.

Dosage : See Package Insert.

© 2004-2018 Amgen Inc. All rights reserved.

Patent : http://pat.amgen.com/sensipar/

Distributed by : Amgen,

One Amgen Center Drive,

Thousand Oaks, CA 91320-1799

Made in Japan